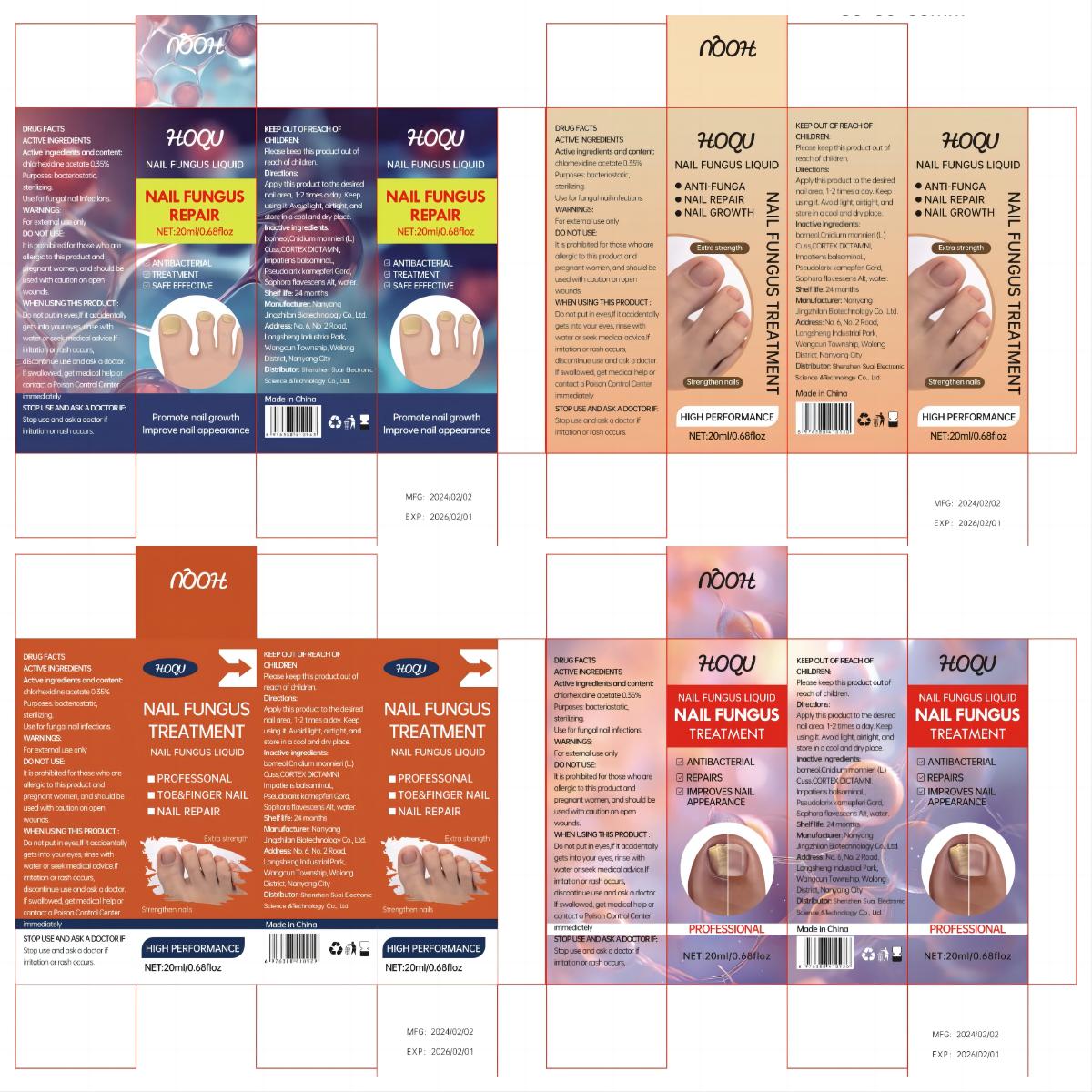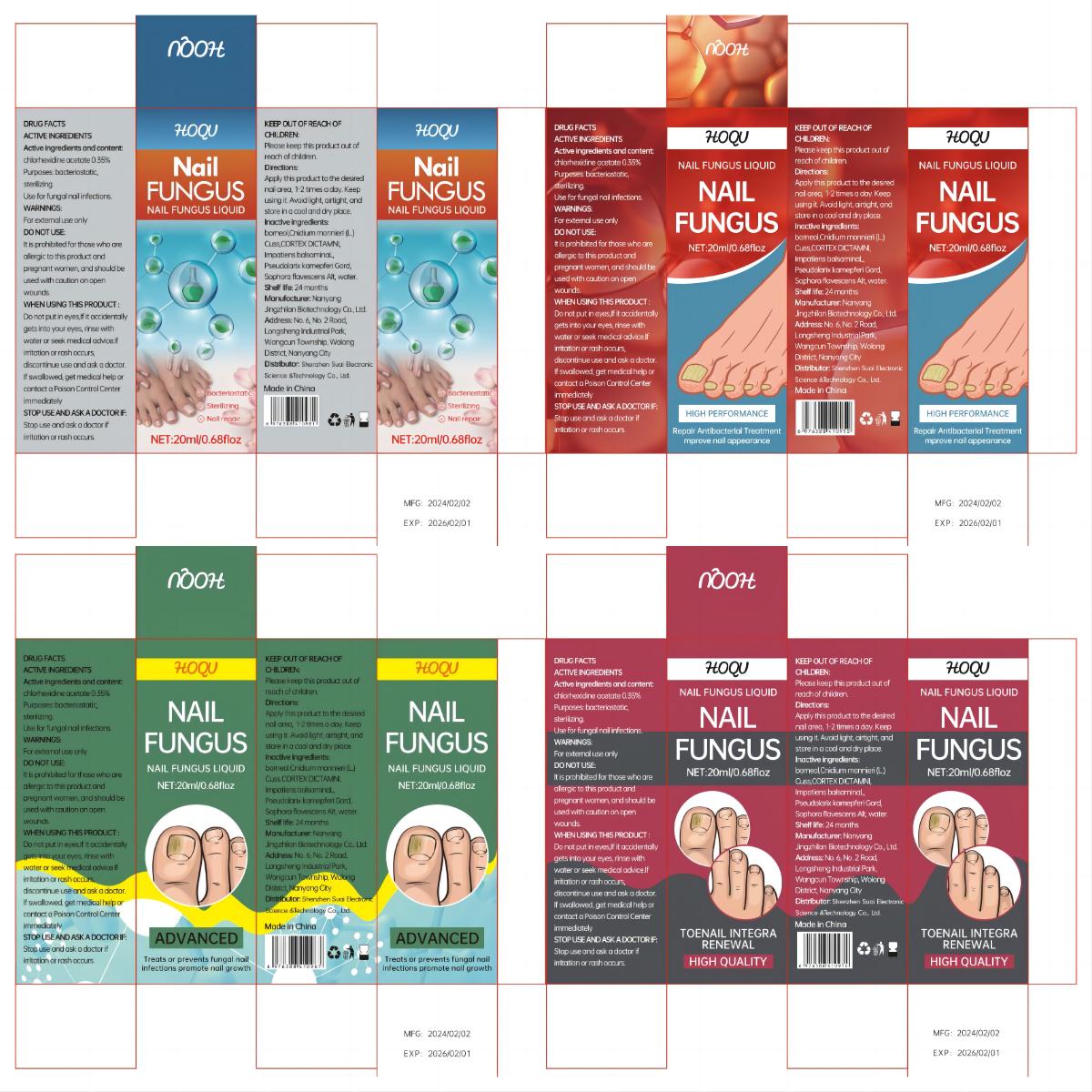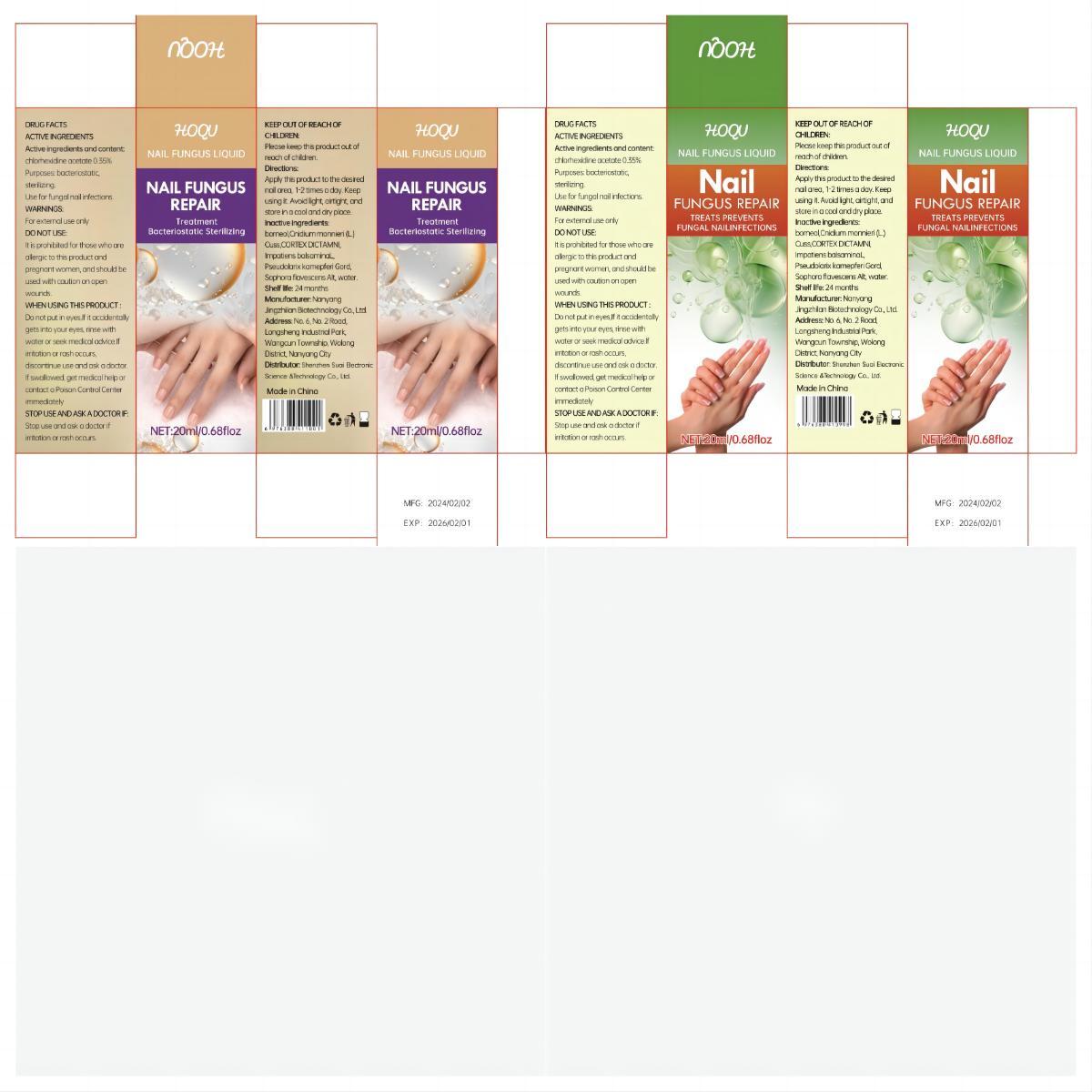 DRUG LABEL: Hoqu Nail Fungus Liquid
NDC: 84095-001 | Form: LIQUID
Manufacturer: Shenzhen Suai Electronic Science & Technology Co., Ltd.
Category: otc | Type: HUMAN OTC DRUG LABEL
Date: 20240218

ACTIVE INGREDIENTS: CHLORHEXIDINE ACETATE 0.35 g/100 mL
INACTIVE INGREDIENTS: IMPATIENS IRVINGII WHOLE; WATER; DICTAMNUS DASYCARPUS ROOT; BORNEOL; CNIDIUM OFFICINALE WHOLE; SOPHORA FLAVESCENS WHOLE; HIBISCUS SYRIACUS BARK

84095-001

Active Ingredient

chlorhexidine acetate 0.35%

Purpose

bacteriostatic, sterilizing.

Use

Use for fungal nail infections.

Warnings

For external use only

Do not use

It is prohibited for those who are allergic to this product and pregnant women, and should be used with caution on open wounds.

When Using

Do not put in eyes,If it accidentally gets into your eyes, rinse with water or seek medical advice.If irritation or rash occurs, discontinue use and ask a doctor. If swallowed, get medical help or contact a Poison Control Center immediately

Stop Use

Stop use and ask a doctor if irritation or rash occurs.

Ask Doctor

Do not put in eyes,lfit accidentally gets into your eyes, rinse with water or seek medical advice.lfirritation or rash occurs, discontinue use and ask a doctor. if swallowed, get medical help orcontact a Poison Control Centerimmediatel

Keep Oot Of Reach Of Children

Please keep this product out of reach of children.

Directions

Apply this product to the desired nail area, 1-2 times a day. Keep using it. Avoid light, airtight, and store in a cool and dry place.

Inactive ingredients

borneol,Cnidium monnieri (L.) Cuss,CORTEX DICTAMNI,Impatiens balsamina L,Pseudolarix kamepferi Gord, Sophora flavescens Alt, water.